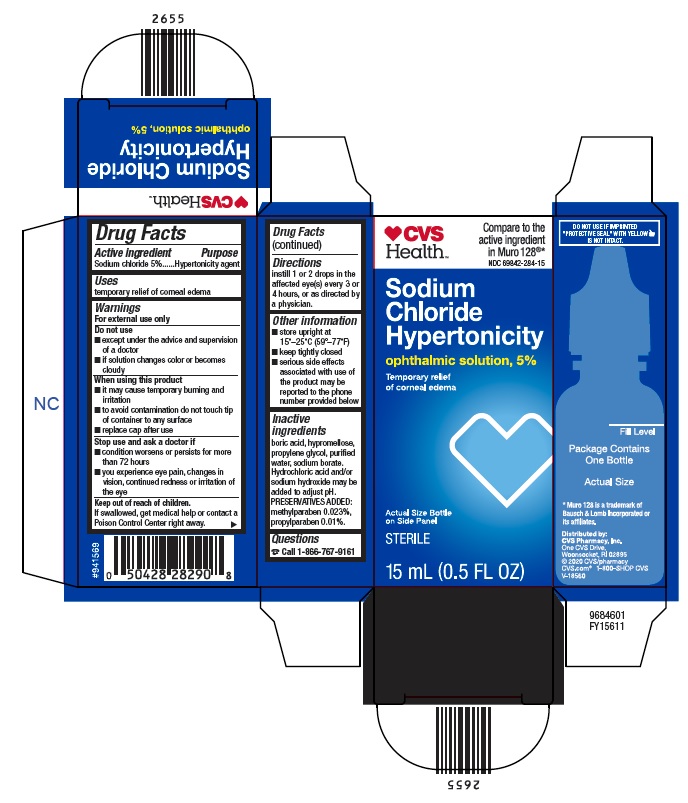 DRUG LABEL: Sodium Chloride Hypertonicity
NDC: 69842-284 | Form: SOLUTION
Manufacturer: CVS Pharmacy
Category: otc | Type: HUMAN OTC DRUG LABEL
Date: 20260115

ACTIVE INGREDIENTS: SODIUM CHLORIDE 50 mg/1 mL
INACTIVE INGREDIENTS: BORIC ACID; HYPROMELLOSE, UNSPECIFIED; PROPYLENE GLYCOL; WATER; SODIUM BORATE; HYDROCHLORIC ACID; SODIUM HYDROXIDE; METHYLPARABEN; PROPYLPARABEN

Drug Facts

Active ingredient

Sodium chloride 5%

Purpose

Hypertonicity agent

Uses

temporary relief of corneal edema

Warnings

For external use only

Do not use
▪ except under the advice and supervision of a doctor
▪ if solution changes color or becomes cloudy

When using this product
▪ it may cause temporary burning and irritation
▪ to avoid contamination do not touch tip of container to any surface
▪ replace cap after use

Stop use and ask a doctor if
▪ condition worsens or persists for more than 72 hours
▪ you experience eye pain, changes in vision, continued redness or irritation of the eye

Keep out of reach of children.

If swallowed, get medical help or contact a Poison Control Center right away.

Directions

instill 1 or 2 drops in the affected eye(s) every 3 or 4 hours, or as directed by a physician.

Other information

▪ store upright at 15°-25°C (59°-77°F)
▪ keep tightly closed
▪ serious side effects associated with use of the product may be reported to the phone number provided below

Inactive ingredients

boric acid, hypromellose, propylene glycol, purified water, sodium borate. Hydrochloric acid and/or sodium hydroxide may be added to adjust pH. PRESERVATIVES ADDED: methylparaben 0.023%, propylparaben 0.01%.

Questions

[phone icon] Call 1-866-767-9161

Package/Label Principal Display Panel

[heart icon] CVS
Health™

Compare to the
active ingredient
in Muro 128®*
NDC 69842-284-15

Sodium
Chloride
Hypertonicity
ophthalmic solution, 5%
Temporary relief
of corneal edema

Actual Size Bottle
on Side Panel

STERILE

15 mL (0.5 FL OZ)